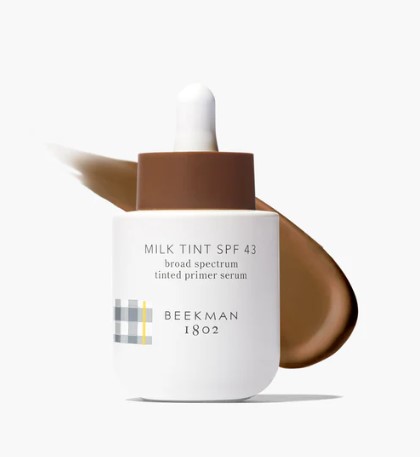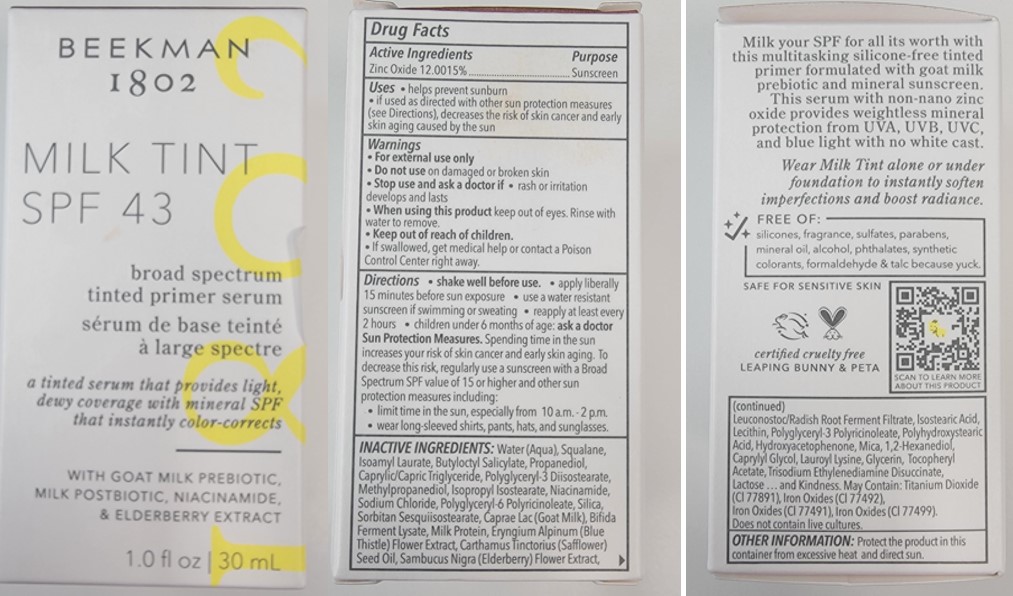 DRUG LABEL: MILK TINT SPF 43 TINTED PRIMER SERUM DEEPEST
NDC: 68577-172 | Form: LOTION
Manufacturer: COSMAX USA, CORPORATION
Category: otc | Type: HUMAN OTC DRUG LABEL
Date: 20241219

ACTIVE INGREDIENTS: ZINC OXIDE 12.0015 mg/100 mg
INACTIVE INGREDIENTS: TRISODIUM ETHYLENEDIAMINE DISUCCINATE; BUTYLOCTYL SALICYLATE; SQUALANE; POLYHYDROXYSTEARIC ACID (2300 MW); ALPHA-TOCOPHEROL ACETATE; POLYGLYCERYL-3 PENTARICINOLEATE; SORBITAN SESQUIISOSTEARATE; MILK PROTEIN; METHYLPROPANEDIOL; ERYNGIUM ALPINUM FLOWER; NIACINAMIDE; SODIUM CHLORIDE; ISOSTEARIC ACID; TITANIUM DIOXIDE; ISOAMYL LAURATE; HYDROXYACETOPHENONE; MICA; 1,2-HEXANEDIOL; CAPRYLYL GLYCOL; LAUROYL LYSINE; CARTHAMUS TINCTORIUS (SAFFLOWER) SEED OIL; LEUCONOSTOC/RADISH ROOT FERMENT FILTRATE; LECITHIN, SUNFLOWER; CAPRYLIC/CAPRIC TRIGLYCERIDE; POLYGLYCERYL-3 DIISOSTEARATE; GOAT MILK; PROPANEDIOL; GLYCERIN; SILICA; POLYGLYCERYL-6 POLYRICINOLEATE; SAMBUCUS NIGRA FLOWER; WATER; ISOPROPYL ISOSTEARATE; LACTOSE; IRON OXIDES

BEEKMAN MILK TINT SPF 43 Tinted Primer Serum DEEPEST

Active Ingredients

Zinc Oxide 12.0015%

Purpose

Sunscreen

USES

- helps prevent sunburn
- if used as directed with other sun protection measures (see Directions), decreases the risk of skin cancer and early skin aging cause by the sun

WARNINGS

For external use only

Do not useon damaged or broken skin

Stop use and ask a doctor if

- rash or irritation develops and lasts

WHEN USING

When using this productkeep out of eyes. Rinse with water to remove.

Keep out of reach of children. If swallowed, get medical help or contact a Poison Control Center right away.

DIRECTIONS

For sunscreen use:

- apply liberally 15 minutes before sun exposure
- use a water resistant sunscreen if swimming or sweating
- reapply at least every 2 hours
- children under 6 months of age: ask a doctor

Sun Protection Measures

Spending time in the sun increases you risk of skin cancer and early skin aging. To decrease this risk, regularly use a sunscreen with a broad spectrum SPF of 15 or higher and other sun protection measures including:

- limit time in the sun, especially from 10 a.m. - 2 p.m.
- wear long-sleeve shirts, pants, hats, and sunglasses

INACTIVE INGREDIENT

Water (Aqua), Squalane, Isoamyl Laurate, Butyloctyl Salicylate, Propanediol, Caprylic/Capric Triglyceride, Polyglyceryl-3 Diisostearate, Methylpropanediol, Isopropyl Isostearate, Niacinamide, Sodium Chloride, Polyglyceryl-6 Polyricinoleate, Silica, Sorbitan Sesquiisostearate, Caprae Lac (Goat Milk), Bifida Ferment Lysate, Milk Protein, Eryngium Alpinum (Blue Thistle) Flower Extract, Carthamus Tinctorius (Safflower) Seed Oil, Sambucus Nigra (Elderberry) Flower Extract, Leuconostoc/Radish Root Ferment Filtrate, Isostearic Acid, Lecithin, Polyglyceryl-3 Polyricinoleate, Polyhydroxystearic Acid, Hydroxyacetophenone, Mica, 1,2-Hexanediol, Caprylyl Glycol, Lauroyl Lysine, Glycerin, Tocopheryl Acetate, Trisodium Ethylenediamine Disuccinate, Lactose May Contain: Titanium Dioxide (CI 77891), Iron Oxides (CI 77492), Iron Oxides (CI 77491), Iron Oxides (CI 77499)